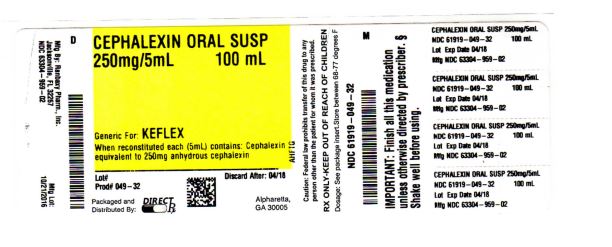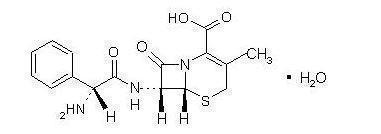 DRUG LABEL: CEPHALEXIN
NDC: 61919-049 | Form: FOR SUSPENSION
Manufacturer: DIRECT RX
Category: prescription | Type: HUMAN PRESCRIPTION DRUG LABEL
Date: 20200117

ACTIVE INGREDIENTS: CEPHALEXIN 250 mg/5 mL
INACTIVE INGREDIENTS: FD&C RED NO. 40; SILICON DIOXIDE; SODIUM BENZOATE; STRAWBERRY; SUCROSE; XANTHAN GUM

CEPHALEXIN

SPL UNCLASSIFIED SECTION

To reduce the development of drug-resistant bacteria and maintain the effectiveness of cephalexin for oral suspension and other antibacterial drugs, cephalexin for oral suspension should be used only to treat or prevent infections that are proven or strongly suspected to be caused by bacteria.

The nucleus of cephalexin is related to that of other cephalosporin antibiotics. The compound is a zwitterion; i.e., the molecule contains both a basic and an acidic group. The isoelectric point of cephalexin in water is approximately 4.5 to 5.

The crystalline form of cephalexin which is available is a monohydrate. It is a white crystalline solid having a bitter taste. Solubility in water is low at room temperature; 1 or 2 mg/mL may be dissolved readily, but higher concentrations are obtained with increasing difficulty.

The cephalosporins differ from penicillins in the structure of the bicyclic ring system.

Cephalexin has a D-phenylglycyl group as substituent at the 7-amino position and an unsubstituted methyl group at the 3-position.

Cephalexin for Oral Suspension, USP, is a pink colored powder forming pink colored suspension on constitution. After mixing, each 5 mL of cephalexin for oral suspension, will contain cephalexin USP equivalent to 125 mg (360 µmol) or 250 mg (720 µmol) of anhydrous cephalexin. The suspension also contains the following inactive ingredients: colloidal silicon dioxide, FD&C Red No. 40, sodium benzoate, strawberry flavor, sucrose, xanthan gum.

DESCRIPTION SECTION

Cephalexin, USP is a semisynthetic cephalosporin antibiotic intended for oral administration. It is 7- (D-α-Amino-α-phenylacetamido)-3-methyl-3-cephem-4-carboxylic acid monohydrate. Cephalexin has the molecular formula C16H17N3O4S • H2O and the molecular weight is 365.41.

Cephalexin has the following structural formula

CLINICAL PHARMACOLOGY SECTION

Human Pharmacology – Cephalexin is acid stable and may be given without regard to meals. It is rapidly absorbed after oral administration. Following doses of 250 mg, 500 mg, and 1 g, average peak serum levels of approximately 9, 18, and 32 mcg/mL respectively were obtained at 1 hour. Measurable levels were present 6 hours after administration. Cephalexin is excreted in the urine by glomerular filtration and tubular secretion. Studies showed that over 90% of the drug was excreted unchanged in the urine within 8 hours. During this period, peak urine concentrations following the 250-mg, 500-mg, and 1-g doses were approximately 1000, 2200, and 5000 mcg/mL respectively.

Microbiology – In vitro tests demonstrate that the cephalosporins are bactericidal because of their inhibition of cell-wall synthesis. Cephalexin has been shown to be active against most strains of the following microorganisms both in vitro and in clinical infections as described in the INDICATIONS AND USAGE section.

Aerobes, Gram-positive:

Staphylococcus aureus (including penicillinase-producing strains)

Staphylococcus epidermidis (penicillin-susceptible strains)

Streptococcus pneumoniae

Streptococcus pyogenes

Aerobes, Gram-negative:

Escherichia coli

Haemophilus influenzae

Klebsiella pneumoniae

Moraxella (Branhamella) catarrhalis

Proteus mirabilis

Note - Methicillin-resistant staphylococci and most strains of enterococci (Enterococcus faecalis [formerly Streptococcus faecalis]) are resistant to cephalosporins, including cephalexin. It is not active against most strains of Enterobacter spp., Morganella morganii, and Proteus vulgaris. It has no activity against Pseudomonas spp. or Acinetobacter calcoaceticus.

Susceptibility Tests –

Diffusion techniques: Quantitative methods that require measurement of zone diameters provide reproducible estimates of the susceptibility of bacteria to antimicrobial compounds. One such standardized procedure1 that has been recommended for use with disks to test the susceptibility of microorganisms to cephalexin uses the 30-mcg cephalothin disk. Interpretation involves correlation of the diameter obtained in the disk test with the minimal inhibitory concentration (MIC) for cephalexin.

Reports from the laboratory providing results of the standard single-disk susceptibility test with a 30-mcg cephalothin disk should be interpreted according to the following criteria:

Zone Diameter (mm) | Interpretation
>18 | (S) Susceptible
15-17 | (I) Intermediate
<14 | (R) Resistant

A report of "Susceptible" indicates that the pathogen is likely to be inhibited by usually achievable concentrations of the antimicrobial compound in blood. A report of "Intermediate" indicates that the result should be considered equivocal, and, if the microorganism is not fully susceptible to alternative, clinically feasible drugs, the test should be repeated. This category implies possible clinical applicability in body sites where the drug is physiologically concentrated or in situations where high dosage of drug can be used. This category also provides a buffer zone that prevents small uncontrolled technical factors from causing major discrepancies in interpretation. A report of "Resistant" indicates that usually achievable concentrations of the antimicrobial compound in the blood are unlikely to be inhibitory and that other therapy should be selected.

Measurement of MIC or MBC and achieved antimicrobial compound concentrations may be appropriate to guide therapy in some infections. (See CLINICAL PHARMACOLOGY section for information on drug concentrations achieved in infected body sites and other pharmacokinetic properties of this antimicrobial drug product.)

Standardized susceptibility test procedures require the use of laboratory control microorganisms.

The 30-mcg cephalothin disk should provide the following zone diameters in these laboratory test quality control strains:

Microorganism | Zone Diameter (mm)
E. coli ATCC 25922 | 15-21
S. aureus ATCC 25923 | 29-37

Dilution techniques: Quantitative methods that are used to determine MICs provide reproducible estimates of the susceptibility of bacteria to antimicrobial compounds. One such standardized procedure uses a standardized dilution method2 (broth, agar, microdilution) or equivalent with cephalothin powder. The MIC values obtained should be interpreted according to the following criteria:

MIC (mcg/mL) | Interpretation
<8 | (S) Susceptible
16 | (I) Intermediate
>32 | (R) Resistant

Interpretation should be as stated above for results using diffusion techniques.

As with standard diffusion techniques, dilution methods require the use of laboratory control microorganisms. Standard cephalothin powder should provide the following MIC values:

Microorganism | MIC (mcg /mL)
E. coli ATCC 25922 | 4-16
S. aureus ATCC 29213 | 0.12-0.5

INDICATIONS & USAGE SECTION

Cephalexin is indicated for the treatment of the following infections when caused by susceptible strains of the designated microorganisms:

Respiratory tract infections caused by S. pneumoniae and S. pyogenes. (Penicillin is the usual drug of choice in the treatment and prevention of streptococcal infections, including the prophylaxis of rheumatic fever. Cephalexin is generally effective in the eradication of streptococci from the nasopharynx; however, substantial data establishing the efficacy of cephalexin in the subsequent prevention of rheumatic fever are not available at present.)

Otitis media due to S. pneumoniae, H. influenzae, staphylococci, streptococci, and M. catarrhalis.

Skin and skin structure infections caused by staphylococci and/or streptococci.

Bone infections caused by staphylococci and/or P. mirabilis.

Genitourinary tract infections, including acute prostatitis, caused by E. coli, P. mirabilis, and K. pneumoniae.

Note – Culture and susceptibility tests should be initiated prior to and during therapy. Renal function studies should be performed when indicated.

To reduce the development of drug-resistant bacteria and maintain the effectiveness of cephalexin for oral suspension and other antibacterial drugs, cephalexin for oral suspension should be used only to treat or prevent infections that are proven or strongly suspected to be caused by susceptible bacteria. When culture and susceptibility information are available, they should be considered in selecting or modifying antibacterial therapy. In the absence of such data, local epidemiology and susceptibility patterns may contribute to the empiric selection of therapy.

CONTRAINDICATIONS SECTION

Cephalexin is contraindicated in patients with known allergy to the cephalosporin group of antibiotics.

WARNINGS SECTION

BEFORE CEPHALEXIN THERAPY IS INSTITUTED, CAREFUL INQUIRY SHOULD BE MADE CONCERNING PREVIOUS HYPERSENSITIVITY REACTIONS TO CEPHALOSPORINS AND PENICILLIN. CEPHALOSPORIN C DERIVATIVES SHOULD BE GIVEN CAUTIOUSLY TO PENICILLIN-SENSITIVE PATIENTS.

SERIOUS ACUTE HYPERSENSITIVITY REACTIONS MAY REQUIRE EPINEPHRINE AND OTHER EMERGENCY MEASURES.

There is some clinical and laboratory evidence of partial cross-allergenicity of the penicillins and the cephalosporins. Patients have been reported to have had severe reactions (including anaphylaxis) to both drugs.

Any patient who has demonstrated some form of allergy, particularly to drugs, should receive antibiotics cautiously. No exception should be made with regard to cephalexin.

Pseudomembranous colitis has been reported with nearly all antibacterial agents, including cephalexin, and may range from mild to life threatening. Therefore, it is important to consider this diagnosis in patients with diarrhea subsequent to the administration of antibacterial agents. Treatment with antibacterial agents alters the normal flora of the colon and may permit overgrowth of clostridia. Studies indicate that a toxin produced by Clostridium difficile is one primary cause of antibiotic-associated colitis.

After the diagnosis of pseudomembranous colitis has been established, appropriate therapeutic measures should be initiated. Mild cases of pseudomembranous colitis usually respond to drug discontinuation alone. In moderate to severe cases, consideration should be given to management with fluids and electrolytes, protein supplementation, and treatment with an antibacterial drug clinically effective against Clostridium difficile colitis.

Usage in Pregnancy – Safety of this product for use during pregnancy has not been established.

PRECAUTIONS SECTION

General – Prescribing cephalexin for oral suspension in the absence of a proven or strongly suspected bacterial infection or a prophylactic indication is unlikely to provide benefit to the patient and increases the risk of the development of drug-resistant bacteria.

Patients should be followed carefully so that any side effects or unusual manifestations of drug idiosyncrasy may be detected. If an allergic reaction to cephalexin occurs, the drug should be discontinued and the patient treated with the usual agents (e.g., epinephrine or other pressor amines, antihistamines, or corticosteroids).

Prolonged use of cephalexin may result in the overgrowth of non-susceptible organisms. Careful observation of the patient is essential. If superinfection occurs during therapy, appropriate measures should be taken.

Positive direct Coombs’ tests have been reported during treatment with the cephalosporin antibiotics. In hematologic studies or in transfusion cross-matching procedures when antiglobulin tests are performed on the minor side or in Coombs’ testing of newborns whose mothers have received cephalosporin antibiotics before parturition, it should be recognized that a positive Coombs’ test may be due to the drug.

Cephalexin should be administered with caution in the presence of markedly impaired renal function. Under such conditions, careful clinical observation and laboratory studies should be made because safe dosage may be lower than that usually recommended.

Indicated surgical procedures should be performed in conjuction with antibiotic therapy.

As a result of administration of cephalexin, a false-positive reaction for glucose in the urine may occur. This has been observed with Benedict’s and Fehling’s solutions and also with Clinitest® tablets. Broad-spectrum antibiotics should be prescribed with caution in individuals with a history of gastrointestinal disease, particularly colitis.

Information for Patients

Patients should be counseled that antibacterial drugs including cephalexin for oral suspension should only be used to treat bacterial infections. They do not treat viral infections (e.g., the common cold). When cephalexin for oral suspension is prescribed to treat a bacterial infection, patients should be told that although it is common to feel better early in the course of therapy, the medication should be taken exactly as directed. Skipping doses or not completing the full course of therapy may (1) decrease the effectiveness of the immediate treatment and (2) increase the likelihood that bacteria will develop resistance and will not be treatable by cephalexin for oral suspension or other antibacterial drugs in the future.

Drug Interactions- Metformin – In healthy subjects given single 500 mg doses of cephalexin and metformin, plasma metformin mean Cmax and AUC increased by an average of 34 % and 24 %, respectively, and metformin mean renal clearance decreased by 14 %. No information is available about the interaction of cephalexin and metformin following multiple doses of either drug.

Although not observed in this study, adverse effects could potentially arise from co-administration of cephalexin and metformin by inhibition of tubular secretion via organic cationic transporter systems. Accordingly, careful patient monitoring and dose adjustment of metformin is recommended in patients concomitantly taking cephalexin and metformin.

Probenicid - As with other β-lactams, the renal excretion of cephalexin is inhibited by probenecid.

Usage in Pregnancy – Pregnancy Category B – The daily oral administration of cephalexin to rats in doses of 250 or 500 mg/kg prior to and during pregnancy, or to rats and mice during the period of organogenesis only, had no adverse effect on fertility, fetal viability, fetal weight, or litter size. Note that the safety of cephalexin during pregnancy in humans has not been established.

Cephalexin showed no enhanced toxicity in weanling and newborn rats as compared with adult animals. Nevertheless, because the studies in humans cannot rule out the possibility of harm, cephalexin should be used during pregnancy only if clearly needed.

Nursing Mothers – The excretion of cephalexin in the milk increased up to 4 hours after a 500-mg dose; the drug reached a maximum level of 4 mcg/mL, then decreased gradually, and had disappeared 8 hours after administration. Caution should be exercised when cephalexin is administered to a nursing woman.

Geriatric Use - Of the 701 subjects in 3 published clinical studies of cephalexin, 433 (62 %) were 65 and over. No overall differences in safety or effectiveness were observed between these subjects and younger subjects, and other reported clinical experience has not identified differences in responses between the elderly and younger patients, but greater sensitivity of some older individuals cannot be ruled out.

This drug is known to be substantially excreted by the kidney, and the risk of toxic reactions to this drug may be greater in patients with impaired renal function. Because elderly patients are more likely to have decreased renal function, care should be taken in dose selection, and it may be useful to monitor renal function (see PRECAUTIONS, General)

ADVERSE REACTIONS SECTION

Gastrointestinal – Symptoms of pseudomembranous colitis may appear either during or after antibiotic treatment. Nausea and vomiting have been reported rarely. The most frequent side effect has been diarrhea. It was very rarely severe enough to warrant cessation of therapy. Dyspepsia, gastritis, and abdominal pain have also occurred. As with some penicillins and some other cephalosporins, transient hepatitis and cholestatic jaundice have been reported rarely.

Hypersensitivity – Allergic reactions in the form of rash, urticaria, angioedema, and, rarely, erythema multiforme, Stevens-Johnson syndrome, or toxic epidermal necrolysis have been observed. These reactions usually subsided upon discontinuation of the drug. In some of these reactions, supportive therapy may be necessary. Anaphylaxis has also been reported.

Other reactions have included genital and anal pruritus, genital moniliasis, vaginitis and vaginal discharge, dizziness, fatigue, headache, agitation, confusion, hallucinations, arthralgia, arthritis, and joint disorder. Reversible interstitial nephritis has been reported rarely. Eosinophilia, neutropenia, thrombocytopenia, and slight elevations in AST and ALT have been reported.

OVERDOSAGE SECTION

Signs and Symptoms – Symptoms of oral overdose may include nausea, vomiting, epigastric distress, diarrhea, and hematuria. If other symptoms are present, it is probably secondary to an underlying disease state, an allergic reaction, or toxicity due to ingestion of a second medication.

Treatment – To obtain up-to-date information about the treatment of overdose, a good resource is your certified Regional Poison Control Center. Telephone numbers of certified poison control centers are listed in the Physicians’ Desk Reference (PDR). In managing overdosage, consider the possibility of multiple drug overdoses, interaction among drugs, and unusual drug kinetics in your patient. Unless 5 to 10 times the normal dose of cephalexin has been ingested, gastrointestinal decontamination should not be necessary.

Protect the patient’s airway and support ventilation and perfusion. Meticulously monitor and maintain, within acceptable limits, the patient’s vital signs, blood gases, serum electrolytes, etc. Absorption of drugs from the gastrointestinal tract may be decreased by giving activated charcoal, which, in many cases, is more effective than emesis or lavage; consider charcoal instead of or in addition to gastric emptying. Repeated doses of charcoal over time may hasten elimination of some drugs that have been absorbed. Safeguard the patient’s airway when employing gastric emptying or charcoal.

Forced diuresis, peritoneal dialysis, hemodialysis, or charcoal hemoperfusion have not been established as beneficial for an overdose of cephalexin; however, it would be extremely unlikely that one of these procedures would be indicated.

The oral median lethal dose of cephalexin in rats is >5,000 mg/kg.

DOSAGE & ADMINISTRATION SECTION

Cephalexin is administered orally.

Adults – The adult dosage ranges from 1 to 4 g daily in divided doses. The usual adult dose is 250 mg every 6 hours. For the following infections, a dosage of 500 mg may be administered every 12 hours: streptococcal pharyngitis, skin and skin structure infections, and uncomplicated cystitis in patients over 15 years of age. Cystitis therapy should be continued for 7 to 14 days. For more severe infections or those caused by less susceptible organisms, larger doses may be needed. If daily doses of cephalexin greater than 4 g are required, parenteral cephalosporins, in appropriate doses, should be considered.

Pediatric Patients – The usual recommended daily dosage for pediatric patients is 25 to 50 mg/kg in divided doses. For streptococcal pharyngitis in patients over 1 year of age and for skin and skin structure infections, the total daily dose may be divided and administered every 12 hours.

Cephalexin Suspension
Weight | 125 mg/ 5 mL
10 kg (22 lb) | ½to 1 tsp q.i.d.
20 kg (44 lb) | 1 to 2 tsp q.i.d.
40 kg (88 lb) | 2 to 4 tsp q.i.d.
Weight | 250 mg/ 5 mL
10 kg (22 lb) | ¼ to ½ tsp q.i.d.
20 kg (44 lb) | ½ to 1 tsp q.i.d.
40 kg (88 lb) | 1 to 2 tsp q.i.d.
or
Weight | 125 mg/ 5 mL
10 kg (22 lb) | 1 to 2 tsp b.i.d.
20 kg (44 lb) | 2 to 4 tsp b.i.d.
40 kg (88 lb) | 4 to 8 tsp b.i.d.
Weight | 250 mg/ 5 mL
10 kg (22 lb) | ½ to 1 tsp b.i.d.
20 kg (44 lb) | 1 to 2 tsp b.i.d.
40 kg (88 lb) | 2 to 4 tsp b.i.d.

In severe infections, the dosage may be doubled.

In the therapy of otitis media, clinical studies have shown that a dosage of 75 to 100 mg/kg/day in 4 divided doses is required.

In the treatment of β-hemolytic streptococcal infections, a therapeutic dosage of cephalexin should be administered for at least 10 days.

Directions for Mixing

For Cephalexin for Oral Suspension, USP 125 mg/5 mL:

Bottle size | Reconstitution directions
100 mL | Add 66 mL of water in two portions to the dry mixture in the bottle. Shake well after each addition
200 mL | Add 132 mL of water in two portions to the dry mixture in the bottle. Shake well after each addition.

For Cephalexin for Oral Suspension, USP 250 mg/5 mL:

Bottle size | Reconstitution directions
100 mL | Add 66 mL of water in two portions to the dry mixture in the bottle. Shake well after each addition.
200 mL | Add 132 mL of water in two portions to the dry mixture in the bottle. Shake

HOW SUPPLIED SECTION

Cephalexin for Oral Suspension, USP, is available in:

The 125 mg per 5 mL oral suspension* is available as follows:

100-mL Bottles NDC 68180-123-01

200-mL Bottles NDC 68180-123-02

The 250 mg per 5 mL oral suspension* is available as follows:

100-mL Bottles NDC 68180-124-01

200-mL Bottles NDC 68180-124-02

————————————————————————————————————

* After mixing, store in a refrigerator. May be kept for 14 days without significant loss of potency.

Shake well before using. Keep tightly closed.

Prior to mixing, store at 20° to 25°C (68° to 77°F) [See USP Controlled Room Temperature].

REFERENCES SECTION

1. National Committee for Clinical Laboratory Standards: Performance standards for antimicrobial disk susceptibility tests-5th ed. Approved Standard NCCLS Document M2-A5, Vol. 13, No. 24, NCCLS, Villanova, PA, 1993.
2. National Committee for Clinical Laboratory Standards: Methods for dilution antimicrobial susceptibility tests for bacteria that grow aerobically-3rd ed. Approved Standard NCCLS Document M7-A3, Vol. 13, No. 25, NCCLS, Villanova, PA, 1993.